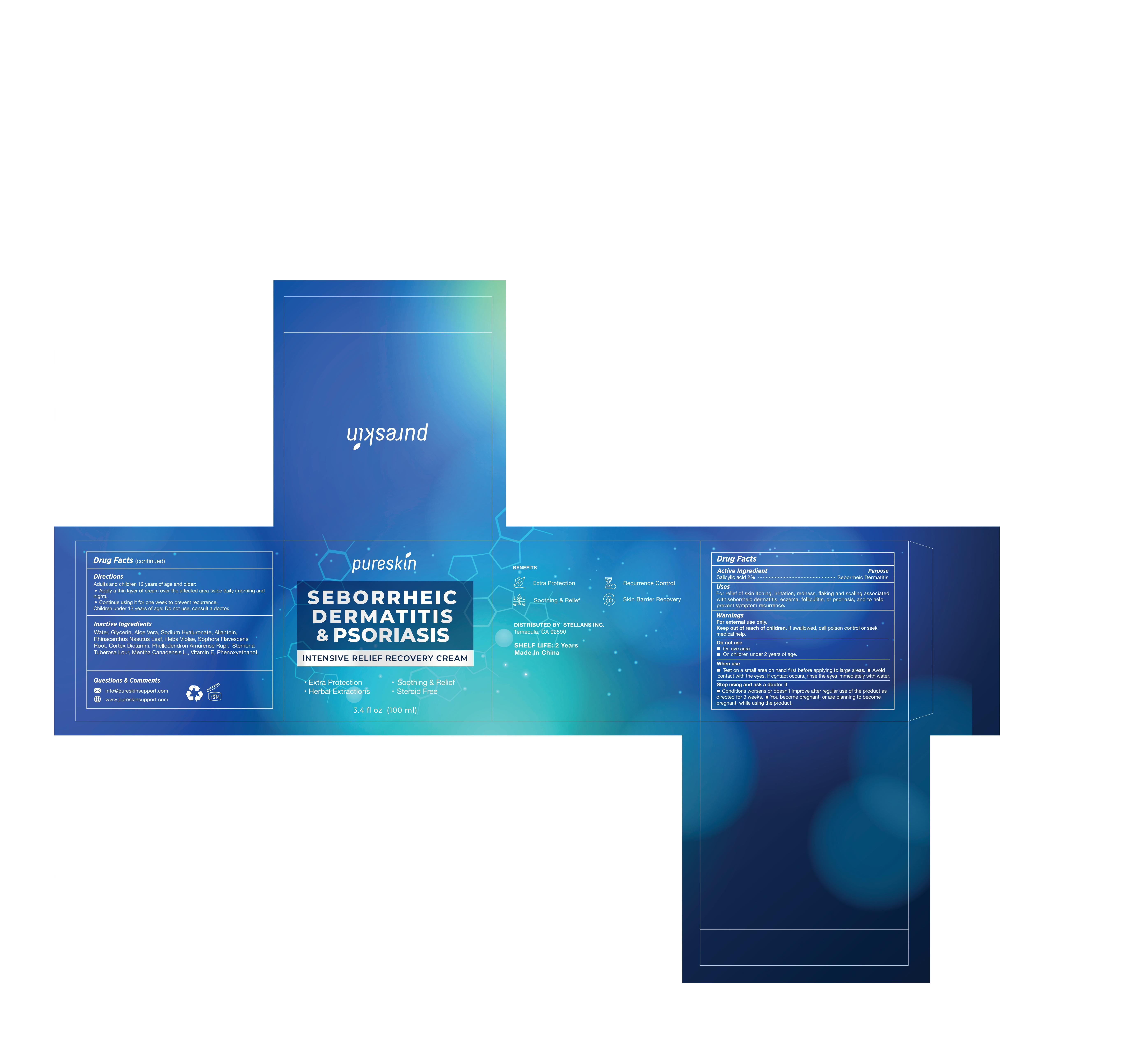 DRUG LABEL: Pureskin Seborrheic Dermatitis Psoriasis Cream
NDC: 83887-007 | Form: CREAM
Manufacturer: Changsha Beiliang E-commerce Co., Ltd
Category: otc | Type: HUMAN OTC DRUG LABEL
Date: 20250603

ACTIVE INGREDIENTS: SALICYLIC ACID 2 g/100 mL
INACTIVE INGREDIENTS: DICTAMNUS DASYCARPUS ROOT; ALPHA-TOCOPHEROL; PHENOXYETHANOL; PHELLODENDRON AMURENSE WHOLE; SODIUM HYALURONATE; WATER; GLYCERIN; ALLANTOIN; RHINACANTHUS NASUTUS LEAF; SOPHORA FLAVESCENS ROOT; VIOLA ADUNCA WHOLE; ALOE VERA LEAF JUICE; STEMONA TUBEROSA WHOLE; MENTHA CANADENSIS WHOLE

83887-007

Active Ingredient

Salicylic Acid 2%

Purpose

seborrheic dermatitis

Use

Help relief of redness, itching, flakin, irritation, associated with seborrheic dermatitis,dandruff,or psoriasis.

Warnings

For external use only.

Do not use

On open skin wounds.
On children less than 2 years of age.

When Using

Avoid contact with eyes. If contact occurs, rinse the eyes immediately with water.
Keep out of the reach of young children.

Stop Use

No improvement after 4 weeks of normal usage.

Ask Doctor

Irritation or rash occurs.

Keep Out Of Reach Of Children

If swallowed, get medical help ot contact a Poison Control Center (1-800-222-1222)right away.

Directions

Clean the affected area with warm water and dry thoroughly.
Apply a thin layer over the affected area two to three times daily and gently massage it 2 minutes, repeat 3 to 5 days after symptoms disappear to control recurrence.
Children should use it under the supervision of adults.

Other information

store at 15-25 ℃

Inactive ingredients

Water, Glycerin, Aloe Vera, Sodium Hyaluronate, Allantoin, Rhinacanthus Nasutus Leaf, Heba Violae, Sophora Flavescens Root, Cortex Dictamni, Phellodendron Amurense Rupr., Stemona Tuberosa Lour, Mentha Canadensis L., Vitamin E, Phenoxyethanol.

Questions

service@pureskinsupport.com
www.pureskinsupport.com